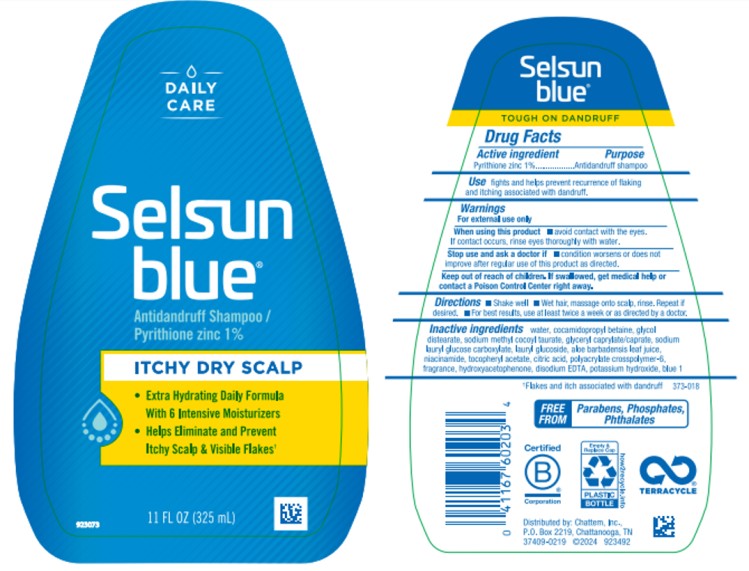 DRUG LABEL: Selsun Blue Itchy Dry Scalp
NDC: 41167-6020 | Form: SHAMPOO
Manufacturer: Chattem, Inc.
Category: otc | Type: HUMAN OTC DRUG LABEL
Date: 20260218

ACTIVE INGREDIENTS: PYRITHIONE ZINC 0.01 g/1 mL
INACTIVE INGREDIENTS: WATER; COCAMIDOPROPYL BETAINE; GLYCOL DISTEARATE; SODIUM METHYL COCOYL TAURATE; LAURYL GLUCOSIDE; GLYCERYL CAPRYLATE/CAPRATE; ALOE VERA LEAF; NIACINAMIDE; .ALPHA.-TOCOPHEROL ACETATE; CITRIC ACID ACETATE; AMMONIUM ACRYLOYLDIMETHYLTAURATE, DIMETHYLACRYLAMIDE, LAURYL METHACRYLATE AND LAURETH-4 METHACRYLATE COPOLYMER, TRIMETHYLOLPROPANE TRIACRYLATE CROSSLINKED (45000 MPA.S); HYDROXYACETOPHENONE; EDETATE DISODIUM; POTASSIUM HYDROXIDE; FD&C BLUE NO. 1

Selsun Blue Dry Itchy Scalp

Drug Facts
Selsun Blue Itchy Dry Scalp

Active ingredient

Pyrithione zinc 1%

Purpose

Antidandruff Shampoo

Use

Fights and help prevent recurrence of flaking and itching associated with dandruff.

Warnings

For external use only

When using this product

- avoid contact with eyes. If contact occurs, rinse eyes thoroughly with water.

Stop use and ask a doctor if

- condition worsens or does not improve after regular use of this product as directed

Keep out of reach of children.

If swallowed, get medical help or contact a Poison Control Center right away.

Directions

- Shake well.
- Wet hair, massage onto scalp, rinse. Repeat if desired.
- For best results, use at least twice a week or as directed by a doctor.

Inactive ingredients

water, cocamidopropyl betaine, glycol distearate, sodium methyl cocoyl taurate, glyceryl caprylate/caprate, sodium lauryl glucose carboxylate, lauryl glucoside, aloe barbadensis leaf juice, niacinamide, tocopheryl acetate, citric acid, polyacrylate crosspolymer-6, fragrance, hydroxyacetophenone, disodium EDTA, potassium hydroxide, blue 1

PRINCIPAL DISPLAY PANEL

DAILY CARE
Selsun
blue®
Antidandruff Shampoo /
Pyrithione zinc 1 %
ITCHY DRY SCALP

11 FL OZ (325 mL)